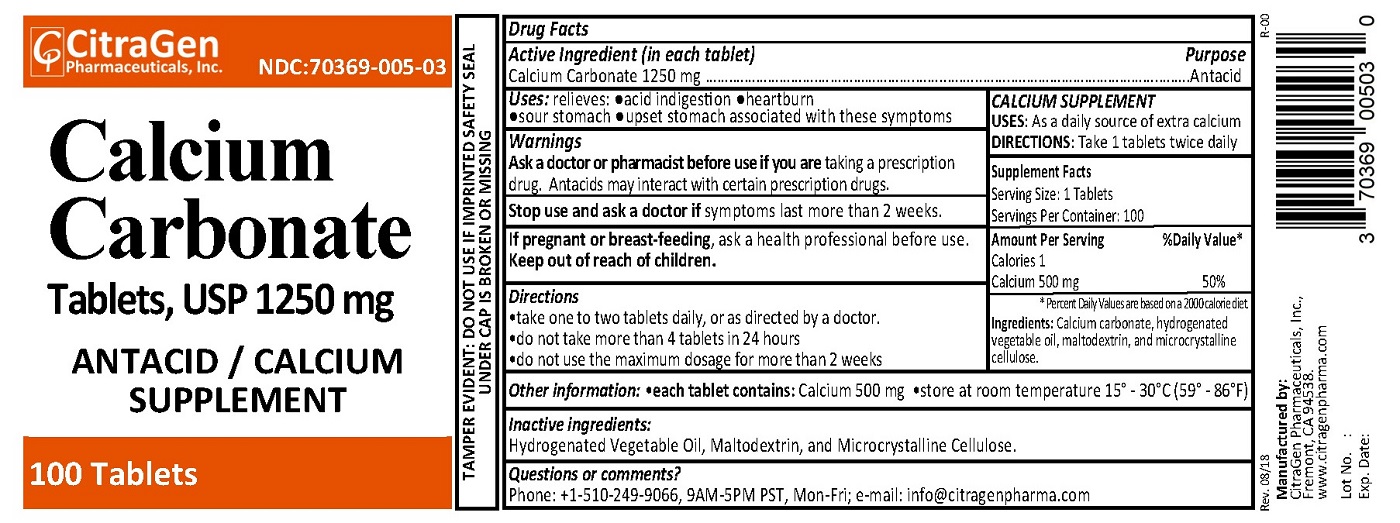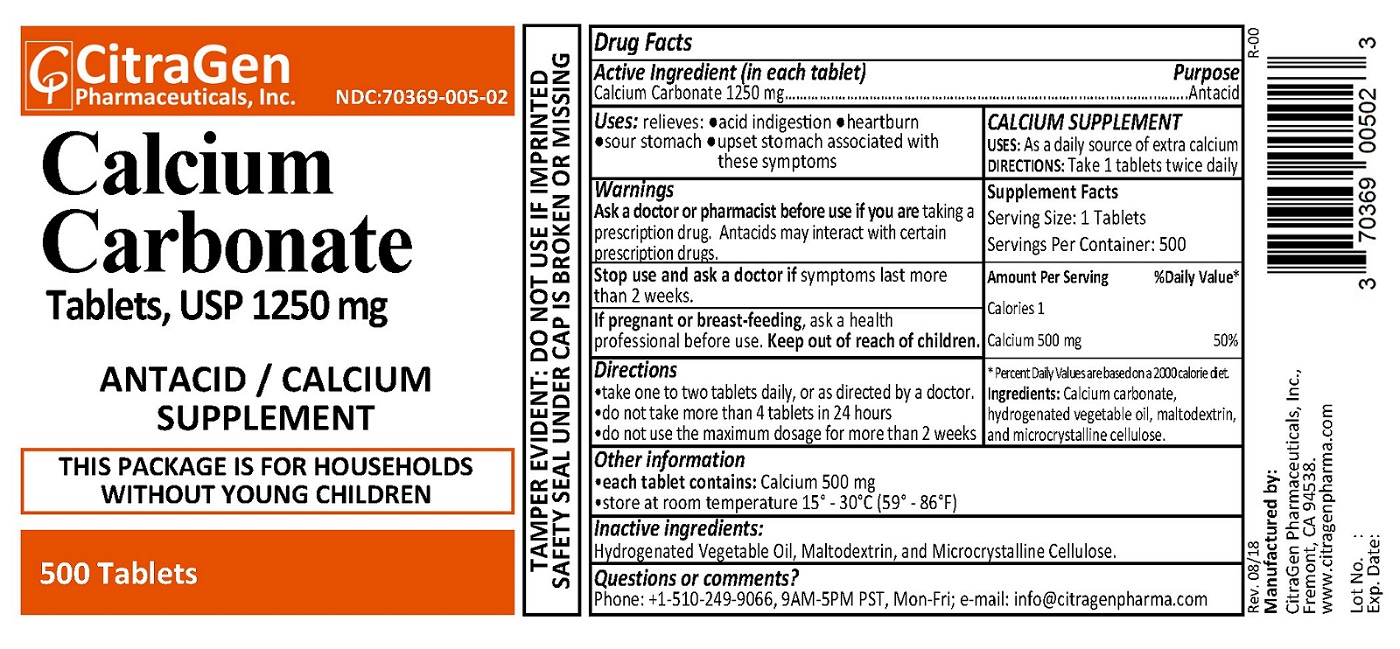 DRUG LABEL: Calcium Carbonate
NDC: 70369-005 | Form: TABLET
Manufacturer: CitraGen Pharmaceuticals, Inc.
Category: otc | Type: HUMAN OTC DRUG LABEL
Date: 20250130

ACTIVE INGREDIENTS: CALCIUM CARBONATE 1250 mg/1 1
INACTIVE INGREDIENTS: HYDROGENATED COTTONSEED OIL; MALTODEXTRIN; CELLULOSE, MICROCRYSTALLINE

Calcium Carbonate Tablets, USP 1250 mg

Drug Facts

Active ingredient (in each tablet)

Calcium carbonate 1250 mg

Purpose

Antacid / Calcium Supplement

Uses

relieves:

- acid indigestion
- heartburn
- sour stomach
- upset stomach associated with these symptoms

Warnings

Ask a doctor or pharmacist before use if you are taking a prescription drug.

Antacids may interact with certain prescription drugs.

Stop use and ask a doctor if symptoms last more than 2 weeks.

PREGNANCY OR BREAST FEEDING

If pregnant or breast-feeding, ask a health professional before use.

Keep out of reach of children.

Directions

- take one to two tablets daily, or as directed by a doctor.
- do not take more than 4 tablets in 24 hours.
- do not use the maximum dosage for more than 2 weeks.

Other information

each tablet contains: Calcium 500 mg

store at room temperature 15º - 30º C (59º - 86º F)

Inactive ingredients

Hydrogenated Vegetable Oil, Maltodextrin and Microcrystalline Cellulose

Questions or comments?

Phone: +1-510-249-9066 (9AM-5PM PST, Mon-Fri); e-mail: info@citragenpharma.com

TAMPER EVIDENT: DO NOT USE IF IMPRINTED SAFETY SEAL UNDER CAP IS BROKEN OR MISSING

Manufactured by:
CitraGen Pharmaceuticals, Inc.,
Fremont, CA 94538.

www.citragenpharma.com

PACKAGE LABEL

CitraGen Pharmaceuticals, Inc.

NDC: 70369-005-02

Rev. 08/18 R-00

Calcium Carbonate Tablets, USP 1250 mg

ANTACID / Calcium Supplement

500 Tablets

THIS PACKAGE IS FOR HOUSEHOLDS WITHOUT YOUNG CHILDREN

PACKAGE LABEL

CitraGen Pharmaceuticals, Inc.

NDC: 70369-005-03

Rev. 08/18 R-00

Calcium Carbonate Tablets, USP 1250 mg

ANTACID / Calcium Supplement

100 Tablets